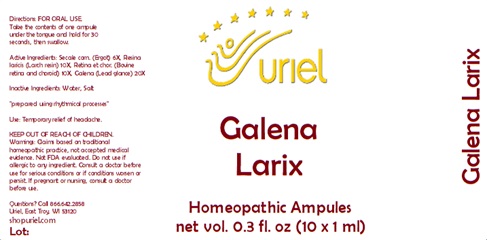 DRUG LABEL: Galena Larix
NDC: 48951-5000 | Form: LIQUID
Manufacturer: Uriel Pharmacy Inc.
Category: homeopathic | Type: HUMAN OTC DRUG LABEL
Date: 20240214

ACTIVE INGREDIENTS: CLAVICEPS PURPUREA SCLEROTIUM 6 [hp_X]/1 mL; LARIX DECIDUA RESIN 10 [hp_X]/1 mL; BOS TAURUS EYE 10 [hp_X]/1 mL; LEAD SULFIDE 20 [hp_X]/1 mL
INACTIVE INGREDIENTS: WATER; SODIUM CHLORIDE

Galena Larix

INDICATIONS AND USAGE

Directions: FOR ORAL USE.

DOSAGE AND ADMINISTRATION

Take the contents of one ampule under the tongue and hold for 30 seconds, then swallow.

ACTIVE INGREDIENT

Active Ingredients: Secale corn. (Ergot) 6X, Resina laricis (Larch resin) 10X, Retina et chor. (Bovine retina and choroid) 10X, Galena (Lead glance) 20X

Inactive Ingredients: Water, Salt

"prepared using rhythmical processes"

PURPOSE

Use: Temporary relief of headache.

KEEP OUT OF REACH OF CHILDREN.

WARNINGS

Warnings: Claims based on traditional homeopathic practice, not accepted medical evidence. Not FDA evaluated. Do not use if allergic to any ingredient. Consult a doctor before use for serious conditions or if conditions worsen or persist. If pregnant or nursing, consult a doctor before use.

QUESTIONS

Questions? Call 866.642.2858 Uriel, East Troy, WI 53120 shopuriel.com Lot: